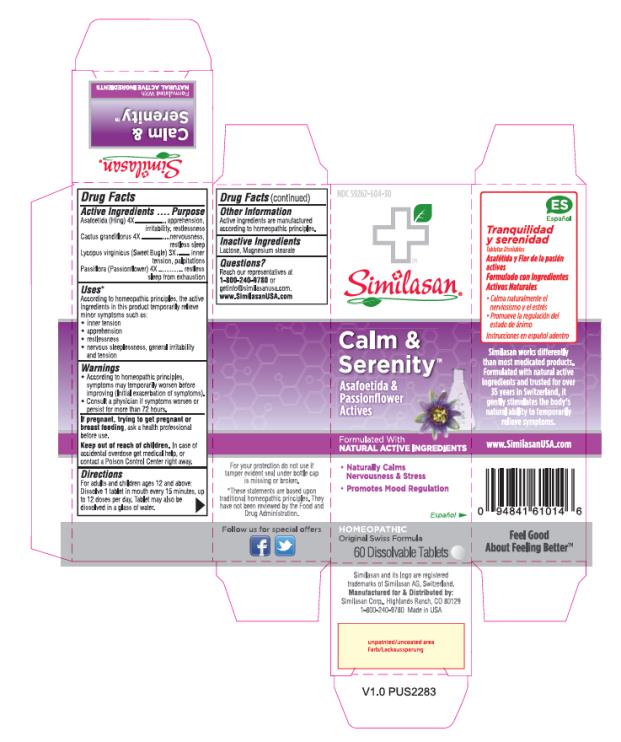 DRUG LABEL: Calm and Serenity
NDC: 59262-604 | Form: TABLET, ORALLY DISINTEGRATING
Manufacturer: Similasan Corporation
Category: homeopathic | Type: HUMAN OTC DRUG LABEL
Date: 20161212

ACTIVE INGREDIENTS: ASAFETIDA 4 [hp_X]/1 1; SELENICEREUS GRANDIFLORUS STEM 4 [hp_X]/1 1; LYCOPUS VIRGINICUS 3 [hp_X]/1 1; PASSIFLORA INCARNATA FLOWERING TOP 4 [hp_X]/1 1
INACTIVE INGREDIENTS: LACTOSE; MAGNESIUM STEARATE

Calm and Serenity

Calm & Serenity

Drug Facts

Active Ingredients

Asafoetida (Hing) 4X

Purpose

apprehension, irritability, restlessness

Active Ingredients

Cactus grandiflorus 4X

Purpose

nervousness, restless sleep

Active Ingredients

Lycopus virginicus (Sweet Bugle) 3X

Purpose

inner tension, palpitations

Active Ingredients

Passiflora (Passionflower) 4X

Purpose

restless sleep from exhaustion

Uses*

According to homeopathic principles, the active ingredients in this product temporarily relieve minor symptoms such as:

• inner tension

• apprehension

• restlessness

• nervous sleeplessness, general irritability and tension

Warnings

• According to homeopathic principles, symptoms may temporarily worsen before improving (Initial exacerbation of symptoms).

• Consult a physician if symptoms worsen or persist for more than 72 hours.

Keep out of reach of children.

In case of accidental overdose get medical help, or contact a Poison Control Center right away.

Directions

For adults and children ages 12 and above:

Dissolve 1 tablet in mouth every 15 minutes, up to 12 doses per day. Tablet may also be dissolved in a glass of water.

Other Information

Active ingredients are manufactured according to homeopathic principles.

Inactive Ingredients

Lactose, Magnesium stearate

Questions?

Reach our representatives at 1-800-240-9780 or getinfo@similasanusa.com.

www.SimilasanUSA.com

*These statements are based upon traditional homeopathic principles. They have not been reviewed by the Food and Drug Administration.

PRINCIPAL DISPLAY PANEL

NDC 59262-604-30
Calm &
Serenity
Asafoetida &
Passionflower
Actives
60 Dissolvable Tablets